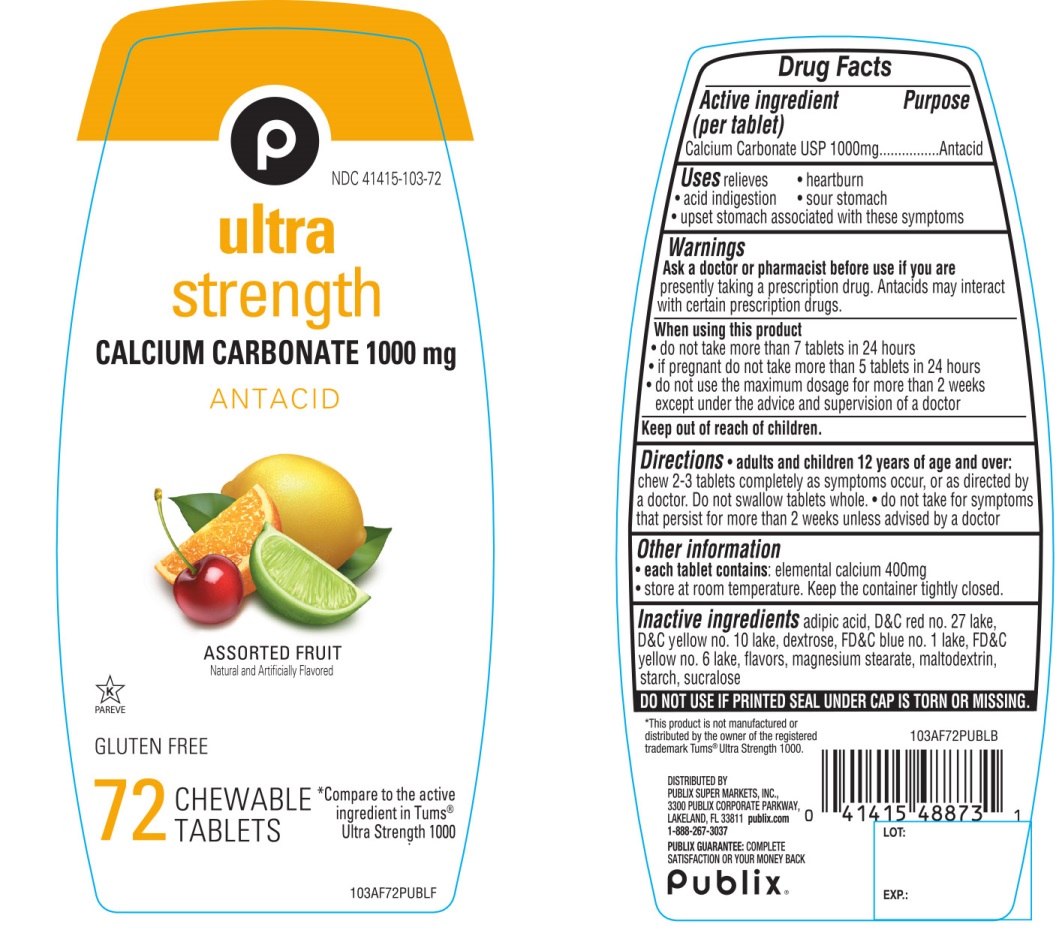 DRUG LABEL: Publix Ultra Strength

NDC: 41415-103 | Form: TABLET, CHEWABLE
Manufacturer: PUBLIX SUPER MARKETS, INC
Category: otc | Type: HUMAN OTC DRUG LABEL
Date: 20251028

ACTIVE INGREDIENTS: CALCIUM CARBONATE 1000 mg/1 1
INACTIVE INGREDIENTS: ADIPIC ACID; D&C RED NO. 27; D&C YELLOW NO. 10; DEXTROSE, UNSPECIFIED FORM; FD&C BLUE NO. 1; FD&C YELLOW NO. 6; MAGNESIUM STEARATE; MALTODEXTRIN; STARCH, CORN; SUCRALOSE

Ultra Strength Antacid Calcium Carbonate 72 Chewable Tablets

Active ingredient (per tablet)

Calcium Carbonate USP 1000mg

Purpose

Antacid

Usage

relieves

- heartburn
- acid indigestion
- sour stomach
- upset stomach associated with these symptoms

Warnings

Ask a doctor or pharmacist before use if you arepresently taking a prescription drug. Antacids may interact with certain prescription drugs.

When using this product

- do not take more than 7 tablets in 24 hours
- if pregnant do not take more than 5 tablets in 24 hours
- do not use the maximum dosage for more than 2 weeks except under the advice and supervision of a doctor.

Directions

- adults and children 12 years of age and over:chew 2-3 tablets as symptoms occur, or as directed by a doctor. Do not swallow tablets whole.
- do not take for symptoms that persist for more than 2 weeks unless advised by a doctor

Other information

- each tablet contains: elemental calcium 400mg
- Store at room temperature. Keep the container tightly closed.

Inactive ingredients

adipic acid, D&C Red # 27 lake, D&C Yellow # 10 lake, dextrose, FD&C Blue # 1 lake, FD&C Yellow # 6 lake, flavors, magnesium stearate, maltodextrin, starch, sucralose.

Questions or comments?

1-888-267-3037

SAFETY SEALED: DO NOT USE IF PRINTED SEAL UNDER CAP IS TORN OR MISSING

Package/Label Principal Display Panel

NDC 41415-103-72

Publix®

Compare to the active ingredient in Tums®Ultra Strength 1000 Assorted Fruit Flavor

ULTRA STRENGTH

CALCIUM CARBONATE 1000 mg

ANTACID

ASSORTED FRUIT

72 CHEWABLE TABLETS

K PAREVE

GLUTEN- FREE

DISTRIBUTED BY:

PUBLIX SUPER MARKETS, INC.,

3300 PUBLIX CORPORATE PARKWAY,

LAKELAND, FL 33811 publix.com

1-888-267-3037

PUBLIX GUARANTEE:COMPLETE SATISFACTION OR YOUR MONEY BACK

*This product is not manufactured or distributed by GlaxoSmithKline LLC, owner of the registered trademark Tums® Ultra Strength.